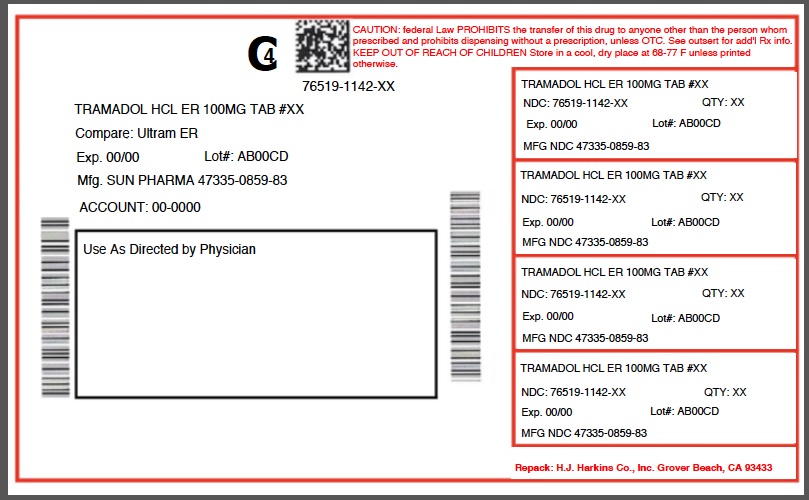 DRUG LABEL: TRAMADOL HYDROCHLORIDE
NDC: 76519-1142 | Form: TABLET, EXTENDED RELEASE
Manufacturer: H.J. Harkins Company, Inc.
Category: prescription | Type: HUMAN PRESCRIPTION DRUG LABEL
Date: 20180816
DEA Schedule: CIV

ACTIVE INGREDIENTS: TRAMADOL HYDROCHLORIDE 100 mg/1 1

1142-03,06

BOXED WARNING

WARNING: ADDICTION, ABUSE, AND MISUSE; LIFE-THREATENING RESPIRATORY DEPRESSION; ACCIDENTAL INGESTION; ULTRA-RAPID METABOLISM OF TRAMADOL AND OTHER RISK FACTORS FOR LIFE-THREATENING RESPIRATORY DEPRESSION IN CHILDREN; NEONATAL OPIOID WITHDRAWAL SYNDROME; INTERACTIONS WITH DRUGS AFFECTING CYTOCHROME P450 ISOENZYMES; AND RISKS FROM CONCOMITANT USE WITH BENZODIAZEPINES OR OTHER CNS DEPRESSANTS
SEE FULL PRESCRIBING INFORMATION FOR COMPLETE BOXED WARNING.

Tramadol hydrochloride extended-release tablets expose users to risks of addiction, abuse, and misuse, which can lead to overdose and death. Assess patient’s risk before prescribing and monitor regularly for these behaviors and conditions. (5.1)
Serious, life-threatening, or fatal respiratory depression may occur. Monitor closely, especially upon initiation or following a dose increase. Instruct patients to swallow tramadol hydrochloride extended-release tablets intact, and not to cut, break, chew, crush, or dissolve the tablets to avoid exposure to a potentially fatal dose of tramadol. (5.2)
Accidental ingestion of tramadol hydrochloride extended-release tablets, especially by children, can result in a fatal overdose of tramadol. (5.2)
Life-threatening respiratory depression and death have occurred in children who received tramadol. Some of the reported cases followed tonsillectomy and/or adenoidectomy; in at least one case, the child had evidence of being an ultra-rapid metabolizer of tramadol due to a CYP2D6 polymorphism (5.3). Tramadol hydrochloride extended-release tablets are contraindicated in children younger than 12 years of age and in children younger than 18 years of age following tonsillectomy and/or adenoidectomy (4). Avoid the use of tramadol hydrochloride extended-release tablets in adolescents 12 to 18 years of age who have other risk factors that may increase their sensitivity to the respiratory depressant effects of tramadol. [see Warnings and Precautions (5.3)]
Prolonged use of tramadol hydrochloride extended-release tablets during pregnancy can result in neonatal opioid withdrawal syndrome, which may be life-threatening if not recognized and treated. If prolonged opioid use is required in a pregnant woman, advise the patient of the risk of neonatal opioid withdrawal syndrome and ensure that appropriate treatment will be available. (5.4)
The effects of concomitant use or discontinuation of cytochrome P450 3A4 inducers, 3A4 inhibitors, or 2D6 inhibitors with tramadol are complex. Use of cytochrome P450 3A4 inducers, 3A4 inhibitors, or 2D6 inhibitors with tramadol hydrochloride extended-release tablets requires careful consideration of the effects on the parent drug, tramadol, and the active metabolite, M1 (5.5, 7)
Concomitant use of opioids with benzodiazepines or other central nervous system (CNS) depressants, including alcohol, may result in profound sedation, respiratory depression, coma, and death. Reserve concomitant prescribing for use in patients for whom alternative treatment options are inadequate; limit dosages and durations to the minimum required; and follow patients for signs and symptoms of respiratory depression and sedation. (5.6, 7)

INDICATIONS AND USAGE

Tramadol hydrochloride is an opioid agonist indicated for the management of pain severe enough to require daily around-the-clock, long-term opioid treatment and for which alternative treatment options are inadequate. (1)
Limitations of Use

Because of the risks of addiction, abuse, and misuse with opioids, even at recommended doses, and because of the greater risks of overdose and death with extended-release opioid formulations, reserve tramadol hydrochloride extended-release tablets for use in patients for whom alternative treatment options (e.g., non-opioid analgesics or immediate-release opioids) are ineffective, not tolerated, or would be otherwise inadequate to provide sufficient management of pain. (1)
Tramadol hydrochloride extended-release tablets are not indicated as an as-needed (prn) analgesic. (1)

DOSAGE AND ADMINISTRATION

To be prescribed only by healthcare providers knowledgeable in use of potent opioids for management of chronic pain. (2.1)
Use the lowest effective dosage for the shortest duration consistent with individual patient treatment goals (2.1).
Individualize dosing based on the severity of pain, patient response, prior analgesic experience, and risk factors for addiction, abuse, and misuse. (2.1)
Do not exceed a daily dose of 300 mg tramadol. Do not use with other tramadol products.(2.1)
For opioid-naïve and opioid non-tolerant patients, initiate tramadol hydrochloride extended-release tablets at a dose of 100 mg once daily, then titrate up by 100 mg increments every 5 days according to need and tolerance. (2.2)
For patients currently on tramadol IR, calculate total 24-hr IR dose, and initiate tramadol hydrochloride extended-release tablets at a dose rounded down to next lower 100 mg increment; then adjust dose according to need and tolerance. See full prescribing information for instructions on conversion, titration, and maintenance of therapy. (2.2, 2.3)
Do not abruptly discontinue tramadol hydrochloride extended-release tablets in a physically-dependent patient. (2.4)

CONTRAINDICATIONS

Children younger than 12 years of age (4)
Postoperative management in children younger than 18 years of age following tonsillectomy and/or adenoidectomy. (4)
Significant respiratory depression (4)
Acute or severe bronchial asthma in an unmonitored setting or in absence of resuscitative equipment (4)
Known or suspected gastrointestinal obstruction, including paralytic ileus (4)
Hypersensitivity to tramadol (4)
Concurrent use of monoamine oxidase inhibitors (MAOIs) or use within the last 14 days (4)

WARNINGS AND PRECAUTIONS

Serotonin Syndrome: Potentially life-threatening condition could result from concomitant serotonergic drug administration. Discontinue tramadol hydrochloride extended-release tablets if serotonin syndrome is suspected. (5.7)
Risk of Seizure: Present within recommended dosage range. Risk is increased with higher than recommended doses and concomitant use of SSRIs, SNRIs, anorectics, tricyclic antidepressants and other tricyclic compounds, other opioids, MAOIs, neuroleptics, other drugs that reduce seizure threshold, in patients with epilepsy or at risk for seizures. (5.8, 7)
Risk of Suicide: Do not use tramadol hydrochloride extended-release tablets in suicidal or addiction-prone patients. Use with caution in those taking tranquilizers, antidepressants or abuse alcohol. (5.9)
Adrenal Insufficiency: If diagnosed, treat with physiologic replacement of corticosteroids, and wean patient off of the opioid. (5.10)
Life-Threatening Respiratory Depression in Patients with Chronic Pulmonary Disease or in Elderly, Cachectic, or Debilitated Patients: Monitor closely, particularly during initiation and titration. (5.11)
Severe Hypotension: Monitor during dosage initiation and titration. Avoid use of tramadol hydrochloride extended-release tablets in patients with circulatory shock. (5.12)
Risks of Use in Patients with Increased Intracranial Pressure, Brain Tumors, Head Injury, or Impaired Consciousness: Monitor for sedation and respiratory depression. Avoid use of tramadol hydrochloride extended-release tablets in patients with impaired consciousness or coma. (5.13)

ADVERSE REACTIONS

Most common adverse reactions (≥10% and ≥2 x placebo rate): Dizziness, constipation, nausea, headache, somnolence, flushing, pruritus, vomiting, insomnia, dry mouth. (6.1)

To report SUSPECTED ADVERSE REACTIONS, contact FDA at 1-800-FDA-1088 or www.fda.gov/medwatch.

DRUG INTERACTIONS

Mixed Agonist/Antagonist and Partial Agonist Opioid Analgesics: Avoid use with tramadol hydrochloride extended-release tablets because they may reduce analgesic effect of tramadol hydrochloride extended-release tablets or precipitate withdrawal symptoms. (5.16,7)

PATIENT COUNSELING INFORMATION

Advise the patient to read the FDA-approved patient labeling (Medication Guide).